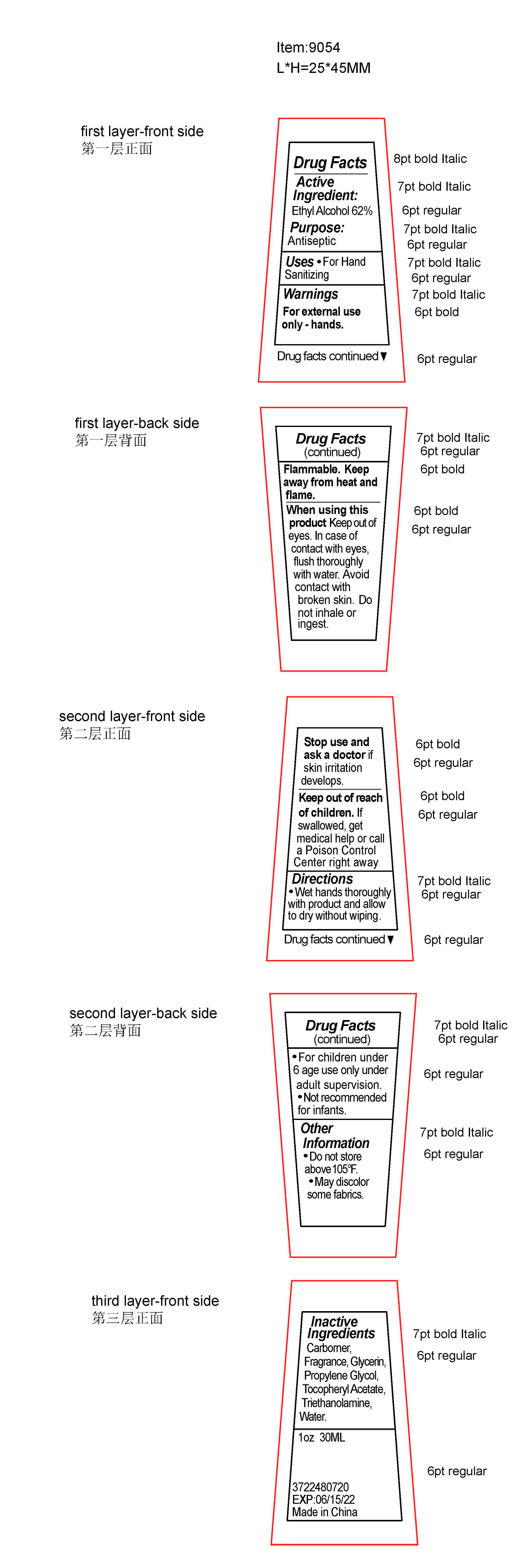 DRUG LABEL: Hand Sanitizer
NDC: 51414-912 | Form: GEL
Manufacturer: Yuyao Jessie Commodity Co., Ltd.
Category: otc | Type: HUMAN OTC DRUG LABEL
Date: 20220318

ACTIVE INGREDIENTS: ALCOHOL 62 mL/100 mL
INACTIVE INGREDIENTS: PROPYLENE GLYCOL; CARBOMER HOMOPOLYMER, UNSPECIFIED TYPE; ALPHA-TOCOPHEROL ACETATE; TROLAMINE; GLYCERIN; WATER

51414-912 HAND SANITIZER Ethyl Alcohol 62%

Active Ingredient(s)

Ethyl Alcohol 62%

Purpose

Antiseptic

Use

for hand sanitizing

Warnings

For external use only.
Flammable, Keep away from heat or flame,
When using this product keep out of eyes, flush thoroughly with water. Avoid contact with broken skin. Do not inhale or ingest.

Stop use and ask a doctor if irritation develops.

Keep out of reach of children. except under adult supervision.

If swallowed, get medical help or call a poison control center right away.

Directions

Wet hands thoroughly with product and allow to dry without wiping.

For children under 6 age use only under adult supervision.

Not recommended for infants.

Inactive ingredients

Carborner,Fragrance,Glycerin,Propylene Glycol,TocopherylAcetate,Triethanolamine,Water.